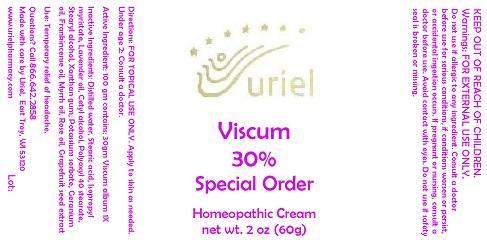 DRUG LABEL: Viscum 30 Special Order
NDC: 48951-9192 | Form: CREAM
Manufacturer: Uriel Pharmacy Inc.
Category: homeopathic | Type: HUMAN OTC DRUG LABEL
Date: 20141204

ACTIVE INGREDIENTS: VISCUM ALBUM FRUITING TOP 1 [hp_X]/1 g
INACTIVE INGREDIENTS: WATER; STEARIC ACID; ISOPROPYL MYRISTATE; LAVENDER OIL; CETYL ALCOHOL; POLYOXYL 40 STEARATE; STEARYL ALCOHOL; XANTHAN GUM; POTASSIUM SORBATE; GERANIUM OIL, ALGERIAN TYPE; FRANKINCENSE OIL; MYRRH OIL; CITRUS PARADISI SEED

Viscum 30 Special Order

INDICATIONS AND USAGE

Directions: FOR TOPICAL USE ONLY.

DOSAGE AND ADMINISTRATION

Apply to skin as needed. Under age 2: Consult a doctor.

Active Ingredient: 100 gm contains: 30gm Viscum album 1X

INACTIVE INGREDIENT

Inactive Ingredients: Distilled water, Stearic acid, Isopropyl myristate, Lavender oil, Cetyl alcohol, Polyoxyl 40 stearate, Stearyl alcohol, Xanthan gum, Potassium sorbate, Geranium oil, Frankincense oil, Myrrh oil, Rose oil, Grapefruit seed extract

PURPOSE

Use: Temporary relief of headache.

KEEP OUT OF REACH OF CHILDREN.

WARNINGS

Warnings: FOR EXTERNAL USE ONLY. Do not use if allergic to any ingredient. Consult a doctor before use for serious conditions, if conditions worsen or persist, or accidental ingestion occurs. If pregnant or nursing, consult a doctor before use. Avoid contact with eyes. Do not use if safety seal is broken or missing.

QUESTIONS

Questions? Call 866.642.2858 Made with care by Uriel, East Troy, WI 53120 www.urielpharmacy.com